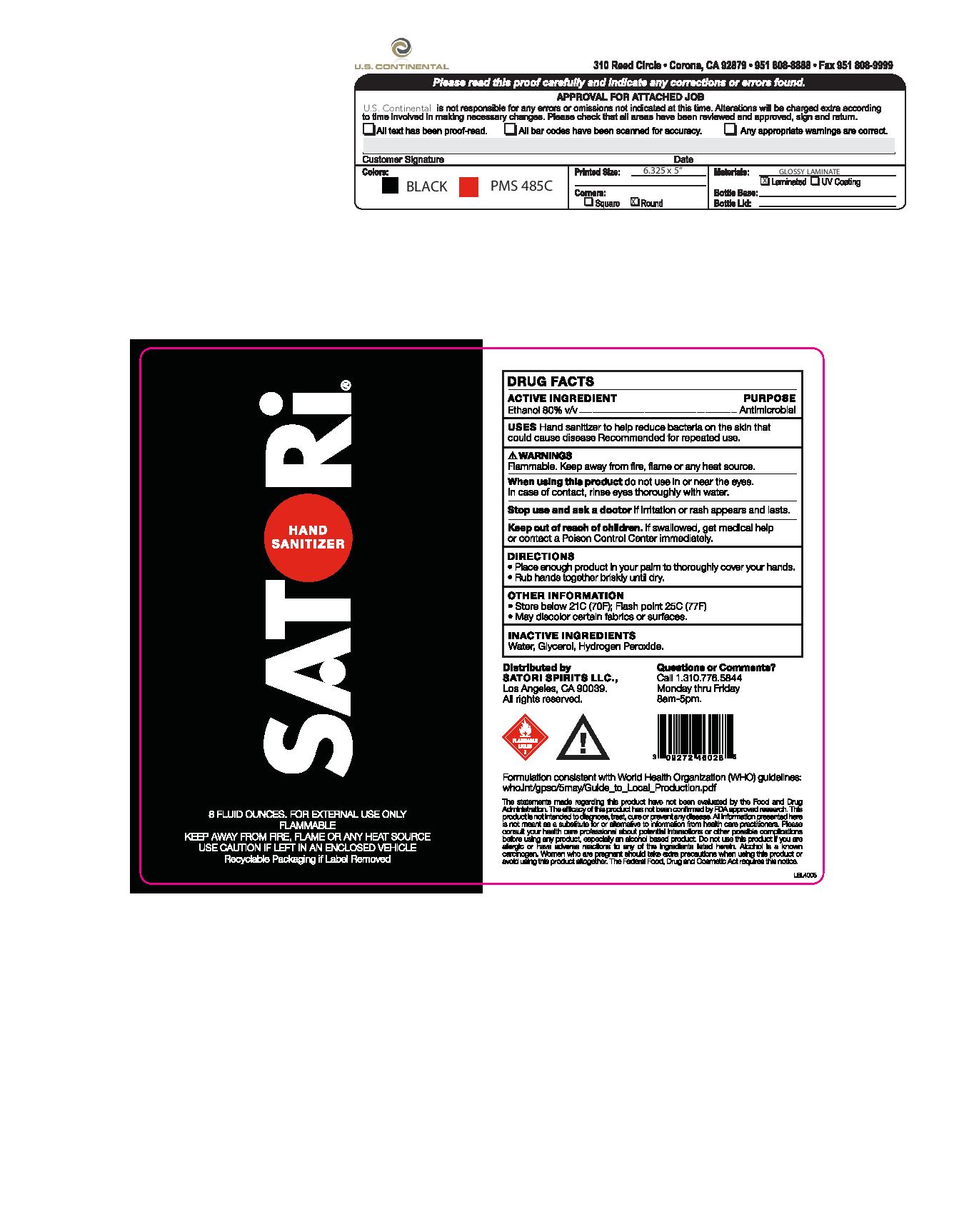 DRUG LABEL: Satori Hand Sanitizer
NDC: 76533-004 | Form: LIQUID
Manufacturer: US Continental
Category: otc | Type: HUMAN OTC DRUG LABEL
Date: 20200724

ACTIVE INGREDIENTS: ALCOHOL 80 mL/100 mL
INACTIVE INGREDIENTS: GLYCERIN 1.45 mL/100 mL; HYDROGEN PEROXIDE 0.125 mL/100 mL; WATER

Active Ingredient(s)

Ethanol 80% v/v.

Purpose

Anitmoicrobial

Use

Hand Sanitizer to help reduce bacteria that potentially can cause disease. Recommended for repeated use.

Warnings

For external use only. Flammable. Keep away from heat or flame

Do not use

- in children less than 2 months of age
- on open skin wounds

When using this product keep out of eyes, ears, and mouth. In case of contact with eyes, rinse eyes thoroughly with water.
Stop use and ask a doctor if irritation or rash occurs. These may be signs of a serious condition.
Keep out of reach of children. If swallowed, get medical help or contact a Poison Control Center right away.

Stop use and ask a doctor if irritation or rash appears or lasts.

Keep out of reach of children. If swallowed, get medical help or contact a Poison Control Center right away.

Directions

- Place enough product on hands to cover all surfaces. Rub hands together until dry.

Other information

- Store below 21C (70F); Flash point 25C (77F)
- may discolour certain fabrics or surfaces

Inactive ingredients

glycerin, hydrogen peroxide, water